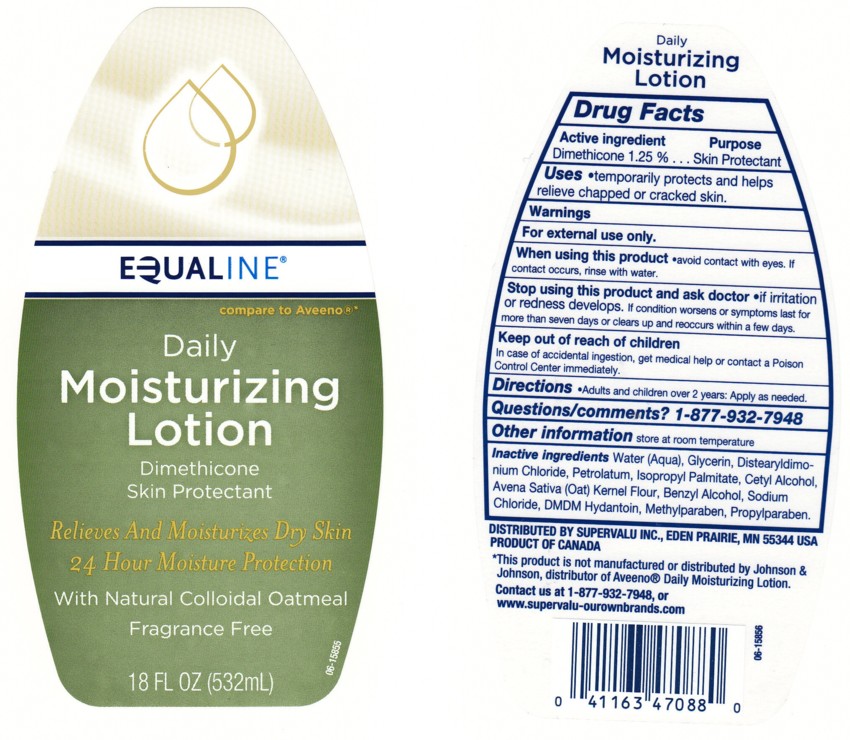 DRUG LABEL: DAILY MOISTURIZING 
NDC: 41163-320 | Form: LOTION
Manufacturer: SUPERVALU INC
Category: otc | Type: HUMAN OTC DRUG LABEL
Date: 20100721

ACTIVE INGREDIENTS: DIMETHICONE 1.25 mL/100 mL

BACK LABEL - DRUG FACTS BOX

ACTIVE INGREDIENT

DIMETHICONE 1.25%

WARNING

FOR EXTERNAL USE ONLY.

When Using This Product

AVOID CONTACT WITH EYES, IF CONTACT OCCURS, RINSE EYE THROUGHLY WITH WATER.

STOP USING THIS PRODUCT AND ASK A DOCTOR IF

CONDITION WORSENS OR SYMPTOMS PERSIST FOR MORE THAN SEVEN DAYS OR OCCUR AGAIN WITHIN A FEW DAYS.

KEEP OUT OF REACH OF CHILDREN

IN CASE OF ACCIDENTAL INGESTION, GET MEDICAL HELP OR CONTACT A POISON CONTROL CENTER IMMEDIATELY.

Purpose

Skin Protectant

QUESTIONS/COMMENTS?

1 - 877 - 932 - 7948

Uses

HELPS PREVENT AND TEMPORARILY PROTECTS CHAFED, CHAPPED OR CRACKED SKIN

Directions

ADULTS AND CHILDREN OVER 2 YEARS: APPLY AS NEEDED.

Inactive Ingredients

Water, Glycerin, Distearyldimonium Chloride, Petrolatum, Isopropyl Palmitate, Cetyl Alcohol, Avena Sativa (Oat) Kernel Flour, Benzyl Alcohol, Sodium Chloride, DMDM Hydantoin, Methylparaben, Propylparaben

Package Front and Back Labels

18OZ Front and Back Labels: equaline18.jpg